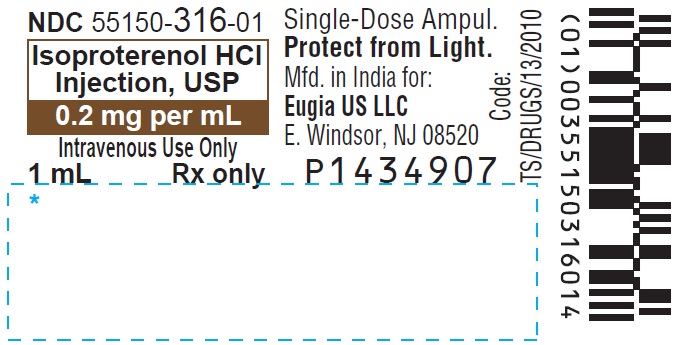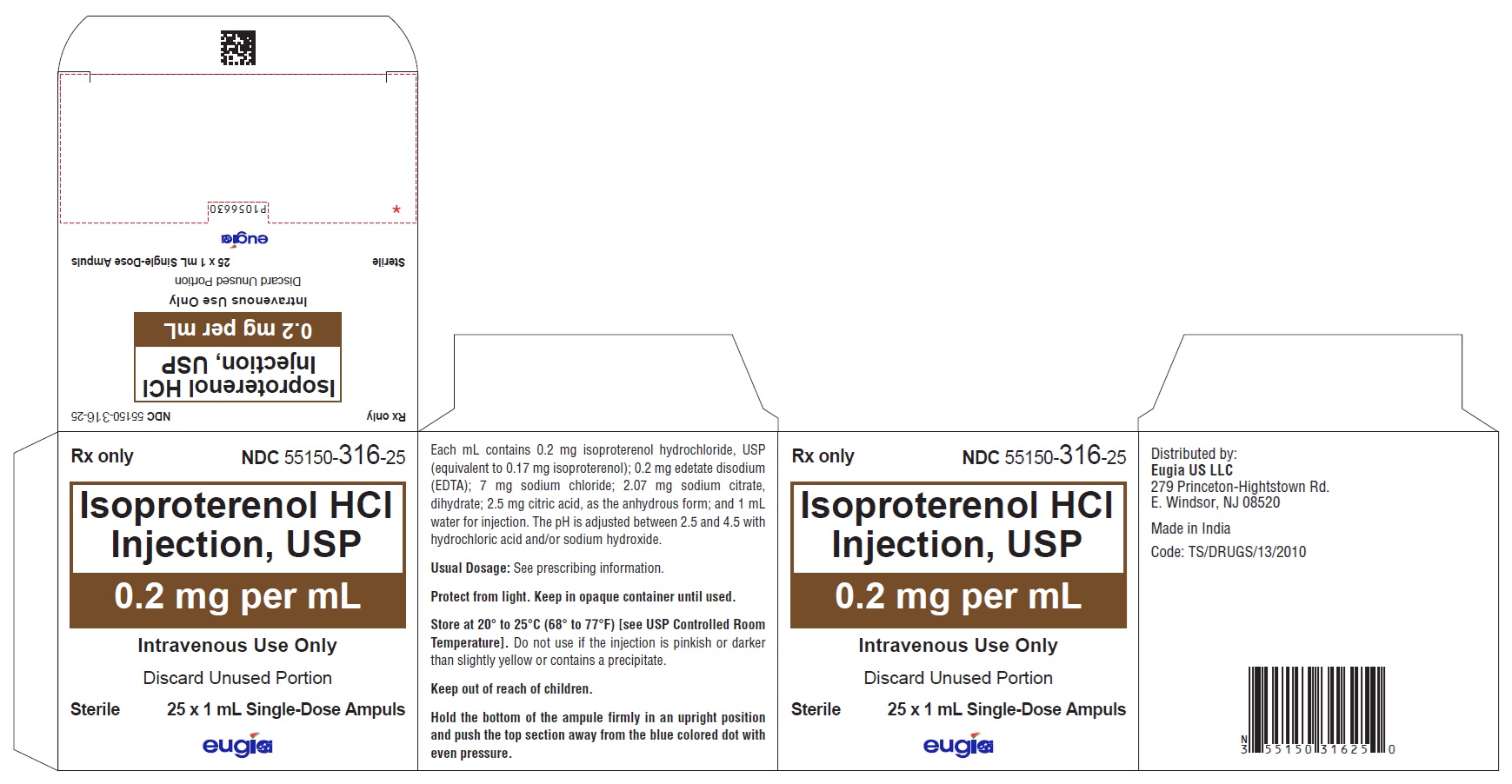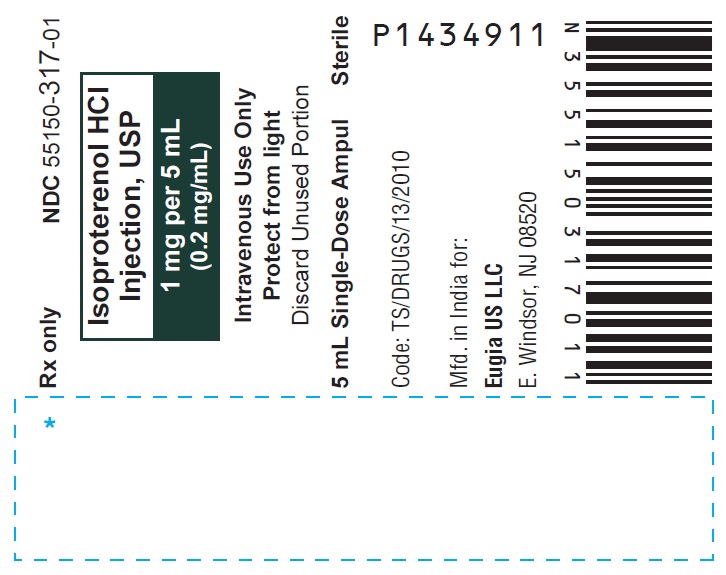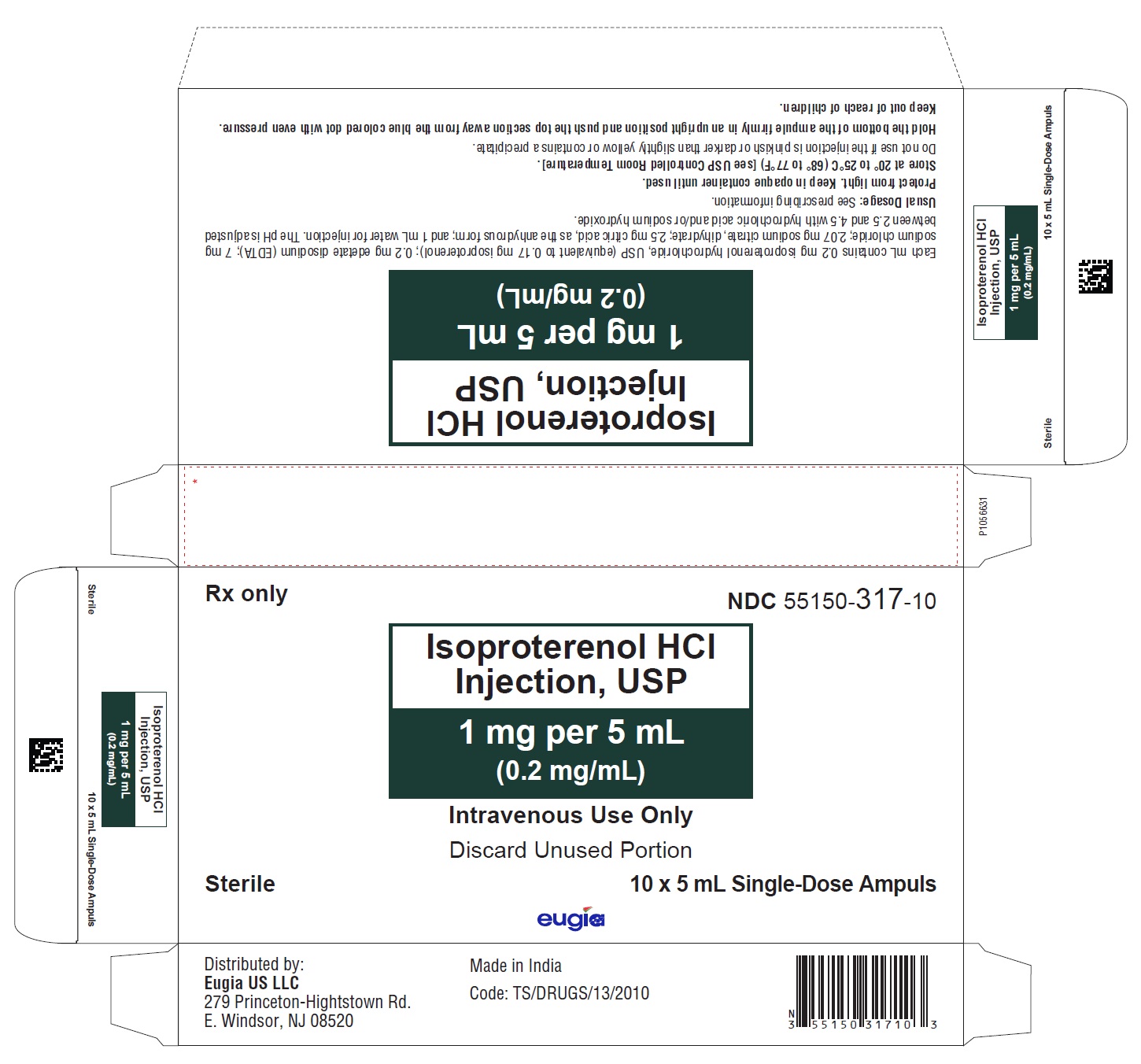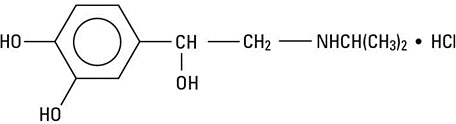 DRUG LABEL: Isoproterenol Hydrochloride
NDC: 55150-316 | Form: INJECTION, SOLUTION
Manufacturer: Eugia US LLC
Category: prescription | Type: Human Prescription Drug Label
Date: 20251216

ACTIVE INGREDIENTS: ISOPROTERENOL HYDROCHLORIDE 0.2 mg/1 mL
INACTIVE INGREDIENTS: EDETATE DISODIUM; SODIUM CHLORIDE; TRISODIUM CITRATE DIHYDRATE; ANHYDROUS CITRIC ACID; WATER; HYDROCHLORIC ACID; SODIUM HYDROXIDE

HIGHLIGHTS OF PRESCRIBING INFORMATION

These highlights do not include all the information needed to use ISOPROTERENOL HYDROCHLORIDE INJECTION safely and effectively. See full prescribing information for ISOPROTERENOL HYDROCHLORIDE INJECTION.
ISOPROTERENOL HYDROCHLORIDE injection, for intravenous use
Initial U.S. Approval: 1956

1 INDICATIONS AND USAGE

Isoproterenol hydrochloride injection is a beta-adrenergic agonist indicated:

- To improve hemodynamic status in patients in distributive shock and shock due to reduced cardiac output (1)
- For treatment of bronchospasm occurring during anesthesia (1)

2 DOSAGE AND ADMINISTRATION

- Initiate isoproterenol hydrochloride injection at the lowest recommended dose and increase gradually based on patient response (2.2)

Recommended initial dosage:

- Shock: 0.5 mcg to 5 mcg per minute as an intravenous infusion (2.2)
- Bronchospasm: 10 mcg to 20 mcg intravenous injection (2.2)

3 DOSAGE FORMS AND STRENGTHS

Injection: 0.2 mg/mL and 1 mg/5 mL (0.2 mg/mL) single-dose ampuls (3)

4 CONTRAINDICATIONS

Isoproterenol hydrochloride is contraindicated in patients with:

- Tachycardia (4)
- Ventricular arrhythmias (4)
- Angina pectoris (4)

5 WARNINGS AND PRECAUTIONS

- Cardiac arrhythmias and ischemia may be induced by isoproterenol hydrochloride (5.1)
- Sulfite: Isoproterenol hydrochloride contains metabisulfite, which may cause allergic reaction (5.2)

6 ADVERSE REACTIONS

Common adverse reactions with isoproterenol include tachycardia and palpitations (6)

To report SUSPECTED ADVERSE REACTIONS, contact Eugia US LLC at 1-866-850-2876 or FDA at 1-800-FDA-1088 or www.fda.gov/medwatch.

7 DRUG INTERACTIONS

- Do not administer isoproterenol hydrochloride and epinephrine simultaneously due to combined effects may induce serious arrhythmias (7)
- Concomitant use of tricyclic antidepressants, monoamine oxidase inhibitors, levothyroxine sodium and certain antihistamines; hemodynamic parameters may potentiate a clinical response of isoproterenol (7)
- Beta-adrenergic blocking drugs may reduce cardiostimulating and bronchodilating effects of isoproterenol (7)

FULL PRESCRIBING INFORMATION

1 INDICATIONS AND USAGE

Isoproterenol hydrochloride injection is indicated:

- To improve hemodynamic status in patients in distributive shock and shock due to reduced cardiac output
- For bronchospasm occurring during anesthesia

2 DOSAGE AND ADMINISTRATION

2.1 General Considerations

Inspect visually for particulate matter and discoloration prior to administration, whenever solution and container permit. Do not use if the injection is pinkish or darker than slightly yellow or contains a precipitate. Discard any unused portion.

Diluted solution should be used immediately. Unused material should be discarded.

2.2 Recommended Dosage

Dosage should generally be started at the lowest recommended dose and increased gradually based on patient response.

Recommended dosage for adults with shock and hypoperfusion states:
Route of Administration | Preparation of Dilution† | Infusion Rate††
Intravenous infusion | Dilute 5 mL (1 mg) in 500 mL of 5% Dextrose Injection, USP | 0.5 mcg to 5 mcg per minute (0.25 mL to 2.5 mL of diluted solution)

†Concentrations up to 10 times greater have been used when limitation of volume is essential.

††Rates over 30 mcg per minute have been used in advanced stages of shock. Adjust the rate of infusion based on heart rate, central venous pressure, systemic blood pressure, and urine flow. If the heart rate exceeds 110 beats per minute, consider decreasing or temporarily discontinuing the infusion.

Recommended dosage for adults with bronchospasm occurring during anesthesia:
Route of Administration | Preparation of Dilution | Initial Dose | Subsequent Dose
Bolus intravenous injection | Dilute 1 mL (0.2 mg) to 10 mL with Sodium Chloride Injection, USP, or 5% Dextrose Injection, USP | 10 mcg to 20 mcg (0.5 mL to 1 mL of diluted solution) | The initial dose may be repeated when necessary

There are no well-controlled studies in children to establish appropriate dosing; however, the American Heart Association recommends an initial infusion rate of 0.1 mcg/kg/min, with the usual range being 0.1 mcg/kg/min to 1 mcg/kg/min.

3 DOSAGE FORMS AND STRENGTHS

Injection solution: single-dose, clear glass ampules containing isoproterenol in a clear, colorless solution;

- 1 mL containing 0.2 mg/1 mL (0.2 mg/mL)
- 5 mL containing 1 mg/5 mL (0.2 mg/mL)

4 CONTRAINDICATIONS

Isoproterenol hydrochloride is contraindicated in patients with:

- tachycardia
- ventricular arrhythmias
- angina pectoris

5 WARNINGS AND PRECAUTIONS

5.1 Cardiac Arrhythmias and Ischemia

Isoproterenol may induce cardiac arrhythmias and myocardial ischemia in patients, especially patients with coronary artery disease, or cardiomyopathy.

5.2 Allergic Reactions associated with Sulfite

Isoproterenol hydrochloride contains sodium metabisulfite, which may cause mild to severe allergic reactions including anaphylaxis or asthmatic episodes, particularly in patients with a history of allergies. However, the presence of metabisulfite in this product should not preclude its use for treatment in emergency situations, even if the patient is sulfite-sensitive, as the alternatives to using isoproterenol in a life- threatening situation may not be satisfactory.

6 ADVERSE REACTIONS

The following adverse reactions have been associated with use of isoproterenol. Because these reactions are reported voluntarily from a population of uncertain size, it is not always possible to estimate their frequency reliably or to establish a causal relationship to drug exposure.

Nervous system disorders: Nervousness, headache, dizziness, visual blurring

Cardiovascular: Tachycardia, tachyarrhythmias, palpitations, angina, ventricular arrhythmias, Adams-Stokes attacks, pulmonary edema

Respiratory: Dyspnea

Other: Flushing of the skin, sweating, mild tremors, pallor, nausea

7 DRUG INTERACTIONS

Table 1. Clinically Relevant Interactions with Isoproterenol
Epinephrine
Clinical Impact | Both drugs are direct cardiac stimulants, and their combined effects may induce serious arrhythmias upon simultaneous administration.
Intervention | Isoproterenol hydrochloride injection and epinephrine should not be administered simultaneously.
Drugsthat maypotentiateclinicalresponseof Isoproterenol
Clinical Impact | The effects of isoproterenol may be potentiated by tricyclic antidepressants, monoamine oxidase inhibitors, levothyroxine sodium,andcertainantihistamines,notablychlorpheniramine, tripelennamine,anddiphenhydramine.
Intervention | Monitor hemodynamic parameters in patients who concurrently are taking tricyclic antidepressants, monoamine oxidase inhibitors, levothyroxine sodium and certain antihistamines. Adjust doses appropriately.
Drugs that may reduce clinical response of Isoproterenol
Clinical Impact | The cardiostimulating and bronchodilating effects of isoproterenol are antagonized by beta-adrenergic blocking drugs, such as propranolol.
Intervention | Monitor for hemodynamic response and relief of bronchospasm and adjust dose appropriately.

8 USE IN SPECIFIC POPULATIONS

8.1 Pregnancy

Risk Summary

Prolonged experience with isoproterenol use in pregnant women over several decades, based on published literature, do not identify a drug associated risk of major birth defects, miscarriage or adverse maternal or fetal outcomes. However, there are risks to the mother and fetus associated with isoproterenol use during labor or delivery (see Clinical Considerations).

The estimated background risk of major birth defects and miscarriage for the indicated population is unknown. All pregnancies have a background risk of birth defect, loss, or other adverse outcomes. In the United States general population, the estimated background risk of major birth defects and miscarriage in clinically recognized pregnancies is 2 to 4% and 15 to 20%, respectively.

Clinical Considerations

Hypotension associated with shock is a medical emergency in pregnancy which can be fatal if left untreated. Delaying treatment in pregnant women with hypotension associated with shock may increase the risk of maternal and fetal morbidity and mortality. Life-sustaining therapy for the pregnant woman should not be withheld due to potential concerns regarding the effects of isoproterenol on the fetus.

Labor and Delivery

Isoproterenol usually inhibits spontaneous or oxytocin induced contractions of the pregnant human uterus and may delay the second stage of labor. Avoid isoproterenol during the second stage of labor. Avoid isoproterenol in obstetrics when maternal blood pressure exceeds 130/80 mmHg.

Although isoproterenol may improve maternal hypotension associated with shock, it may result in uterine vasoconstriction, decreased uterine blood flow, uterine atony with hemorrhage, and fetal anoxia.

8.2 Lactation

Risk Summary

There is no information regarding the presence of isoproterenol in milk or the effects of isoproterenol on the breastfed infant or on milk production. However, due to its short half-life, isoproterenol exposure is expected to be very low in the breastfed infant.

8.4 Pediatric Use

Safety and efficacy of isoproterenol in pediatric patients have not been established.

Intravenous infusions of isoproterenol in refractory asthmatic children at rates of 0.05 to 2.7 mcg/kg/min have caused clinical deterioration, myocardial necrosis, congestive heart failure and death. The risks of cardiac toxicity appear to be increased by some factors [acidosis, hypoxemia, coadministration of corticosteroids, coadministration of methylxanthines (theophylline, theobromine) or aminophylline] that are especially likely to be present in these patients. If intravenous isoproterenol is used in children with refractory asthma, patient monitoring must include continuous assessment of vital signs, frequent electrocardiography, and daily measurements of cardiac enzymes, including CPK-MB.

8.5 Geriatric Use

Clinical studies of isoproterenol hydrochloride did not include sufficient numbers of subjects aged 65 and over to determine whether they respond differently from younger subjects in clinical circumstances. There are, however, some data that suggest that elderly healthy or hypertensive patients are less responsive to beta-adrenergic stimulation than are younger subjects. In general, dose selection for elderly patients should be cautious, usually starting at the low end of the dosing range, reflecting the greater frequency of decreased hepatic, renal or cardiac function and of concomitant diseases or other drug therapy.

10 OVERDOSAGE

Overdosage of isoproterenol can cause tachycardia or other arrhythmias, palpitations, angina, hypotension, or hypertension. In case of overdosage, reduce the rate of administration or discontinue isoproterenol hydrochloride injection until patient’s condition stabilizes. Monitor blood pressure, pulse, respiration, and EKG.

It is not known whether isoproterenol hydrochloride is dialyzable.

11 DESCRIPTION

Isoproterenol hydrochloride injection, USP is 3,4-Dihydroxy-α-[(isopropylamino)methyl] benzyl alcohol hydrochloride, a synthetic sympathomimetic amine that is structurally related to epinephrine but acts almost exclusively on beta receptors. Isoproterenol hydrochloride is white to practically white, crystalline powder and the molecular formula is C11H17NO3 ·HCl. It has a molecular weight of 247.72 and the following structural formula:

Isoproterenol hydrochloride, USP is a racemic compound.

Each milliliter of the sterile solution contains:
Isoproterenolhydrochloride,USP (equivalent to Isoproterenol 0.17 mg) | 0.2 mg
Edetate Disodium (EDTA) | 0.2 mg
Sodium Citrate Dihydrate | 2.07 mg
Citric Acid, Anhydrous | 2.5 mg
Sodium Chloride | 7 mg
Water for Injection | qs 1 mL

The pH is adjusted between 2.5 and 4.5 with hydrochloric acid and/or sodium hydroxide.

The sterile solution is nonpyrogenic clear, colorless or practically colorless liquid free from visible particles and can be administered by the intravenous route.

12 CLINICAL PHARMACOLOGY

12.1 Mechanism of Action

Isoproterenol is a potent nonselective beta-adrenergic agonist with very low affinity for alpha-adrenergic receptors.

12.2 Pharmacodynamics

Intravenous infusion of isoproterenol in man lowers peripheral vascular resistance, primarily in skeletal muscle but also in renal and mesenteric vascular beds. Diastolic pressure falls. Renal blood flow is decreased in normotensive subjects but is increased markedly in shock. Systolic blood pressure may remain unchanged or rise, although mean arterial pressure typically falls. Cardiac output is increased because of the positive inotropic and chronotropic effects of the drug in the face of diminished peripheral vascular resistance.

Isoproterenol relaxes almost all varieties of smooth muscle when the tone is high, but this action is most pronounced on bronchial and gastrointestinal smooth muscle. It prevents or relieves bronchoconstriction, but tolerance to this effect develops with overuse of the drug.

In man, isoproterenol causes less hyperglycemia than does epinephrine. Isoproterenol and epinephrine are equally effective in stimulating the release of free fatty acids and energy production.

12.3 Pharmacokinetics

Absorption

Isoproterenol is readily absorbed when given parenterally or as an aerosol.

Elimination

Isoproterenol is metabolized primarily in the liver and other tissues by COMT. Isoproterenol is a relatively poor substrate for MAO and is not taken up by sympathetic neurons to the same extent as are epinephrine and norepinephrine. The duration of action of isoproterenol may therefore be longer than that of epinephrine but is still brief.

13 NONCLINICAL TOXICOLOGY

13.1 Carcinogenesis, Mutagenesis, Impairment of Fertility

Long-term studies in animals to evaluate the carcinogenic potential of isoproterenol hydrochloride have not been done. Mutagenic potential and effect on fertility have not been determined. There is no evidence from human experience that isoproterenol hydrochloride injection may be carcinogenic or mutagenic or that it impairs fertility.

16 HOW SUPPLIED/STORAGE AND HANDLING

Isoproterenol hydrochloride injection, USP is a sterile, nonpyrogenic, clear, colorless or practically colorless liquid free from visible particles and is supplied as follows:

0.2 mg per mL:
1 mL Single-Dose Ampuls in a Carton of 25 55150-316-25

1 mg per 5 mL (0.2 mg/mL):

5 mL Single-Dose Ampuls in a Carton of 10 55150-317-10

Protect from light. Keep in opaque container until used.

Store at 20º to 25ºC (68º to 77ºF) [see USP Controlled Room Temperature].

Do not use if the injection is pinkish or darker than slightly yellow or contains a precipitate.

Discard unused portion.

Distributed by:
Eugia US LLC
279 Princeton-Hightstown Rd.
E. Windsor, NJ 08520

Manufactured by:
Eugia Pharma Specialities Limited
Hyderabad - 500032
India

PACKAGE LABEL-PRINCIPAL DISPLAY PANEL - 0.2 mg per mL - 1 mL Ampule Label

NDC 55150-316-01
Isoproterenol HCl
Injection, USP
0.2 mg per mL
Intravenous Use Only
1 mL Rx only

PACKAGE LABEL-PRINCIPAL DISPLAY PANEL – 0.2 mg per mL - 1 mL Container-Carton [25 Ampules]

Rx only NDC 55150-316-25
Isoproterenol HCl
Injection, USP
0.2 mg per mL
Intravenous Use Only
Discard Unused Portion
Sterile 25 x 1 mL Single-Dose Ampuls
eugia

PACKAGE LABEL-PRINCIPAL DISPLAY PANEL - 1 mg per 5 mL (0.2 mg / mL) - 5 mL Ampule Label

Rx only NDC 55150-317-01
Isoproterenol HCl
Injection, USP
1 mg per 5 mL
(0.2 mg/mL)
Intravenous Use Only
Protect form light
Discard Unused Portion
5 mL Single-Dose Ampul Sterile
Code: TS/DRUGS/13/2010
Mfd. in India for:
Eugia US LLC
E. Windsor, NJ 08520
eugia

PACKAGE LABEL-PRINCIPAL DISPLAY PANEL – 1 mg per 5 mL (0.2 mg / mL) - 5 mL Container-Carton [10 Ampules]

Rx only NDC 55150-317-10
Isoproterenol HCl
Injection, USP
1 mg per 5 mL
(0.2 mg/mL)
Intravenous Use Only
Discard Unused Portion
Sterile 10 x 5 mL Single-Dose Ampuls
eugia